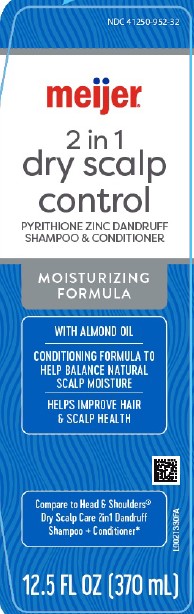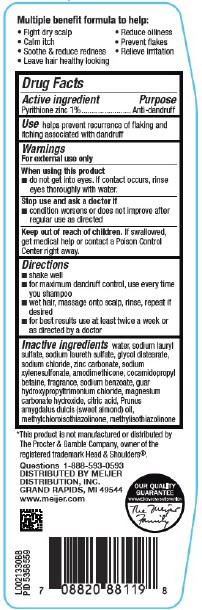 DRUG LABEL: Dry Scalp
NDC: 41250-952 | Form: SHAMPOO
Manufacturer: Meijer, Inc.
Category: otc | Type: HUMAN OTC DRUG LABEL
Date: 20260219

ACTIVE INGREDIENTS: PYRITHIONE ZINC 10 mg/1 mL
INACTIVE INGREDIENTS: WATER; SODIUM LAURYL SULFATE; SODIUM LAURETH SULFATE; GLYCOL DISTEARATE; SODIUM CHLORIDE; ZINC CARBONATE; SODIUM XYLENESULFONATE; AMODIMETHICONE (800 CST); COCAMIDOPROPYL BETAINE; SODIUM BENZOATE; GUAR HYDROXYPROPYLTRIMONIUM CHLORIDE (1.7 SUBSTITUENTS PER SACCHARIDE); MAGNESIUM CARBONATE HYDROXIDE; CITRIC ACID MONOHYDRATE; ALMOND OIL; METHYLCHLOROISOTHIAZOLINONE; METHYLISOTHIAZOLINONE

Meijer 296.007/296AT-AW
Dandruff Shampoo, Dry Scalp 2 in 1

Claims

Multiple benefit formula to help:

- Fight dry scalp
- Calm itch
- Soothe & reduce redness
- Leave hair healthy looking
- Reduce oiliness
- Prevent flakes
- Relieve irritation

Active ingredient

Pyrithione zinc 1%

Purpose

Anti-Dandruff

Use

helps prevent recurrence of flaking and itching associated with dandruff

Warnings

For external use only

When using this product

- do not get into eyes. If contact occurs, rinse eyes thoroughly with water.

Stop use and ask a doctor if

- condition worsens or does not improve after regular use as directed

Keep out of reach of children.

If swallowed, get medical help or contact a Poison Control Center right away.

Directions

- shake well
- for maximum dandruff control, use every time you shampoo
- wet hair, massage onto scalp, rinse, repeat if desired
- for best results at least twice a week or as directed by a doctor

Inactive ingredients

water, sodium lauryl sulfate, sodium laureth sulfate, glycol distearate, sodium chloride, zinc carbonate, sodium xlenesulfonate, amodimethicone, cocamidopropyl betaine, fragrance, sodium benzoate, guar hydroxypropyltrimonium chloride, magnesium carbonate hydroxide, citric acid, prunus amygdalus dulcis (sweet almond) oil, methylchloroisothiazolinone, methylisothiazolinone

Disclaimer

*This product is not manufactured or distributed by Procter & Gamble Company, owner of the registered trademark Head & Shoulders®.

Adverse Reactions

Questions 1-888-593-0593

DISTRIBUTED BY

MEIJER DISTRIBUTION, INC.

GRAND RAPIDS, MI 49544

www.meijer.com

OUR QUALITY GUARANTEE

WWW.MEIJER.COM.SATISFACTION

The Meijer Family

Principal display panel

NDC 41250-952-32

meijer®

2 in 1

dry scalp control

PYRITHIONE ZINC DANDRUFF

SHAMPOO & CONDITIONER

MOISTURIZING FORMULA

WITH ALMOND OIL

CONDITIONING FORMULA TO HELP BALANCE NATURAL SCALP MOISTURE

HELPS IMPROVE HAIR & SCALP HEALTH

Compare to Head & Shoulders®Dry Scalp Care 2in1 Dandruff Shampoo + Conditioner*

12.5 FL OZ (370 mL)